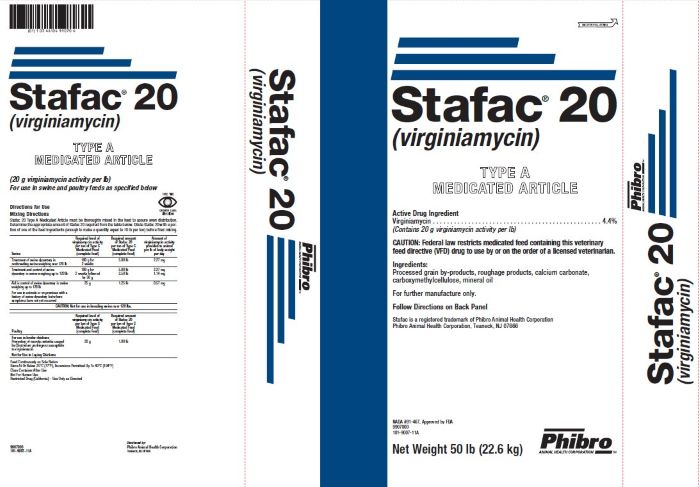 DRUG LABEL: Stafac 20
NDC: 66104-1220 | Form: POWDER
Manufacturer: Phibro Animal Health
Category: animal | Type: VFD TYPE A MEDICATED ARTICLE ANIMAL DRUG LABEL
Date: 20251010

ACTIVE INGREDIENTS: VIRGINIAMYCIN 20 g/0.45 kg
INACTIVE INGREDIENTS: RICE BRAN

Stafac® 20
(virginiamycin)
TYPE A MEDICATED ARTICLE

Active Drug Ingredient

Virginiamycin . . . . . . . . . . . . . . . . . . . . . . . . . . . . . . . . . . . . . . . . 4.4%

(Contains 20 g virginiamycin activity per lb)

CAUTION:

Federal law restricts medicated feed containing this veterinary feed directive (VFD) drug to use by or on the order of a licensed veterinarian.

Ingredients:

Processed grain by-products, roughage products, calcium carbonate,

carboxymethylcellulose, mineral oil

INDICATIONS AND USAGE

(20 g virginiamycin activity per lb)

For use in swine and poultry feeds as specified below

Directions for Use

Mixing Directions

Stafac 20 Type A Medicated Article must be thoroughly mixed in the feed to assure even distribution. Determine the appropriate amount of Stafac 20 required from the table below. Dilute Stafac 20 with a portion of one of the feed ingredients (enough to make a quantity equal to 10 lb per ton) before final mixing.

Swine | Required level of virginiamycin activity per ton of Type C Medicated Feed (complete feed) | Required amount of Stafac 20 per ton of Type C Medicated Feed (complete feed) | Amount of virginiamycin activity provided to animal per lb of body weight per day
Treatment of swine dysentery in nonbreeding swine weighing over 120 lb | 100 g for; 2 weeks | 5.00 lb | 2.27 mg
Treatment and control of swine dysentery in swine weighing up to 120 lb | 100 g for; 2 weeks followed by 50g | 5.00 lb; 2.50 lb | 2.27 mg; 1.14 mg
Aid in control of swine dysentery in swine weighing up to 120 lb; For use in animals or on premises with a history of swine dysentery but where symptoms have not yet occurred | 25 g | 1.25 lb | 0.57 mg
CAUTION: Not for use in breeding swine over 120 lbs.
Poultry | Required level of virginiamycin activity per ton of Type C Medicated Feed (complete feed) | Required amount of Stafac 20 per ton of Type C Medicated Feed (complete feed)
Prevention of necrotic enteritis caused by Clostridium perfringens susceptible to virginiamycin; Not for Use in Laying Chickens | 20 g | 1.00 lb

Feed Continuously as Sole Ration

Store at Or Below 25oC (77oF), Excursions Permitted Up To 40oC (104oF)

Close Container After Use

For further manufacture only.

Follow Directions on Back Panel

Stafac is a registered trademark of Phibro Animal Health Corporation

Phibro Animal Health Corporation, Teaneck, NJ 07666

Net Weight 50 lb (22.6 kg)

Approved by FDA under NADA # 091-467

9907000

101-9007-12

Stafac 20